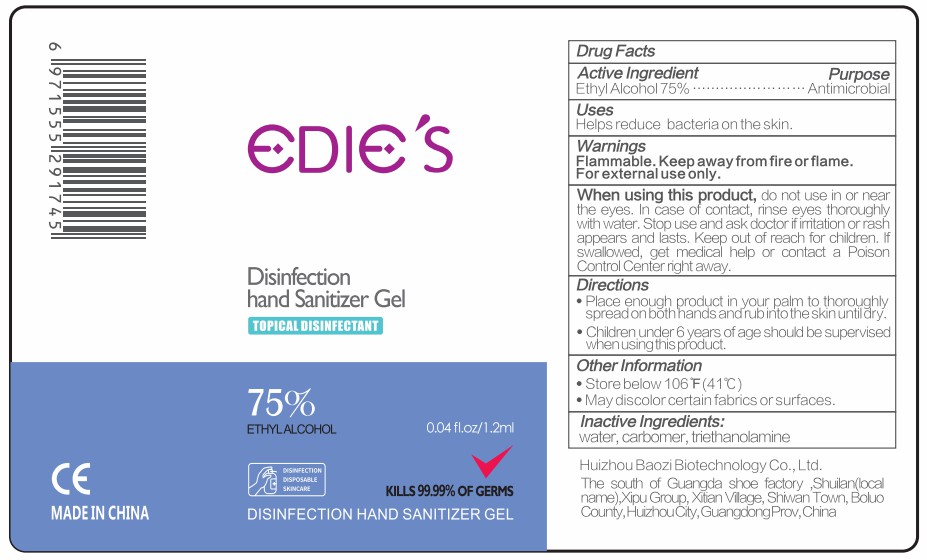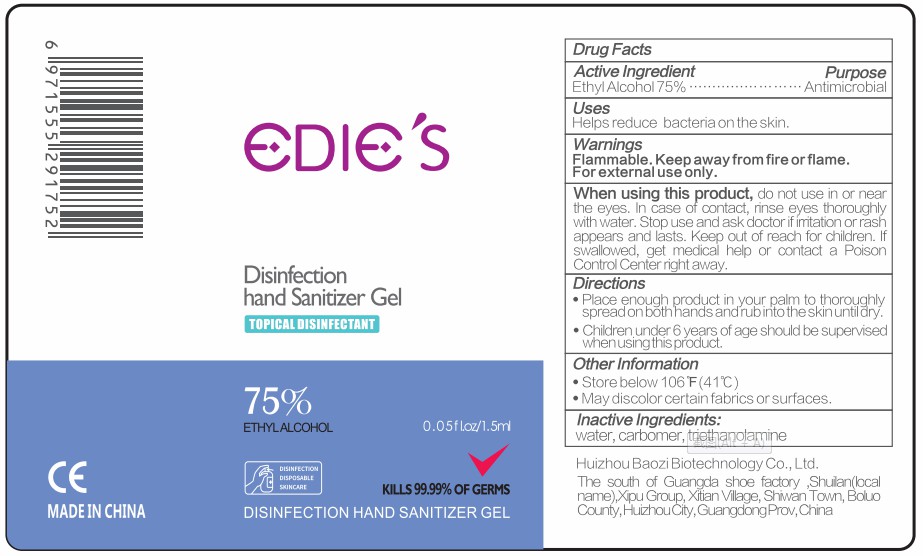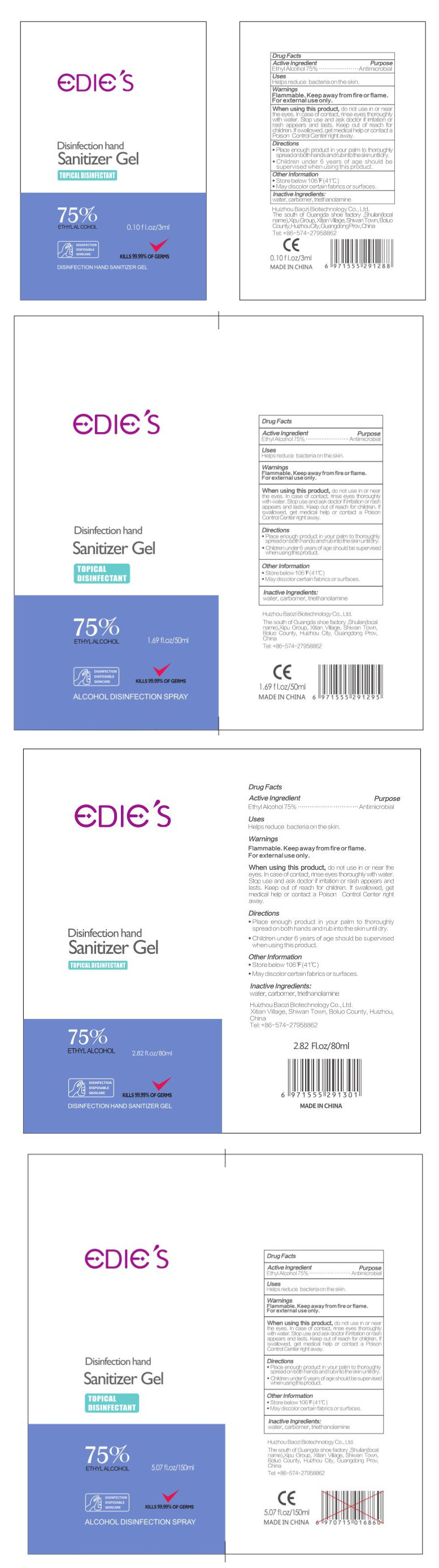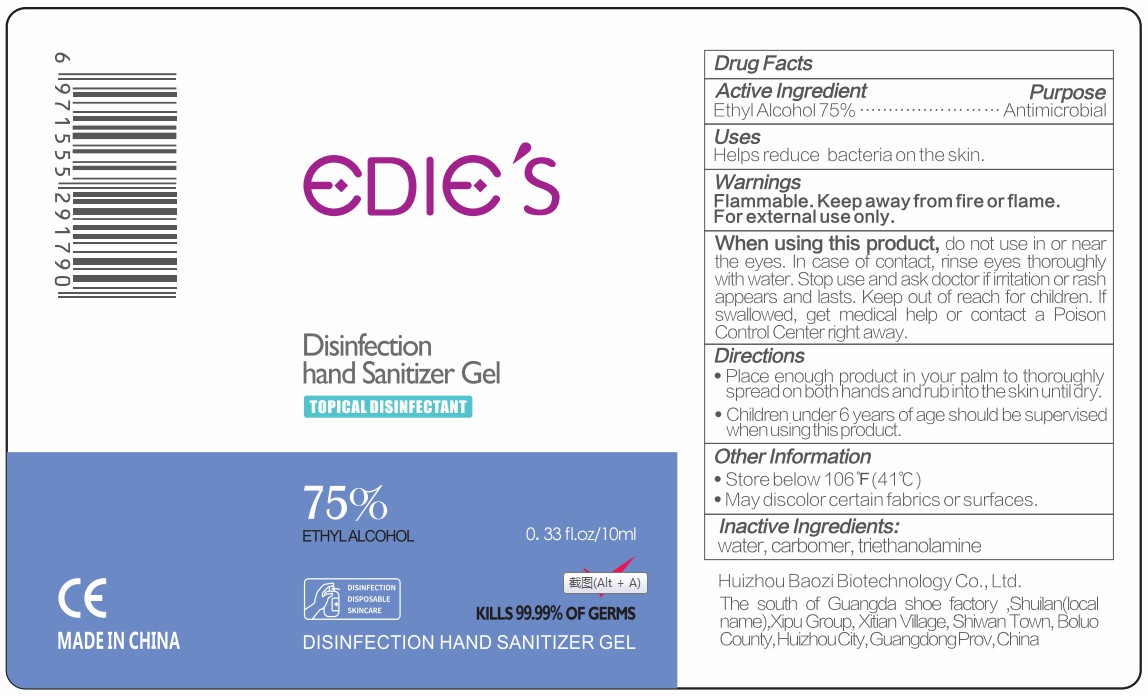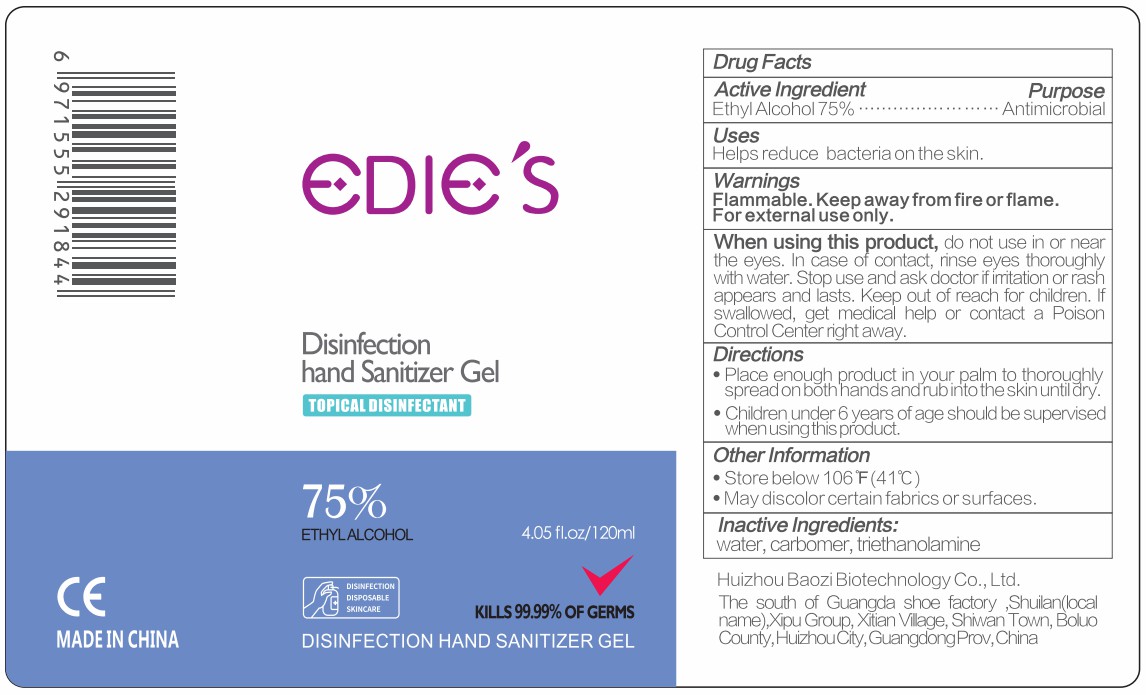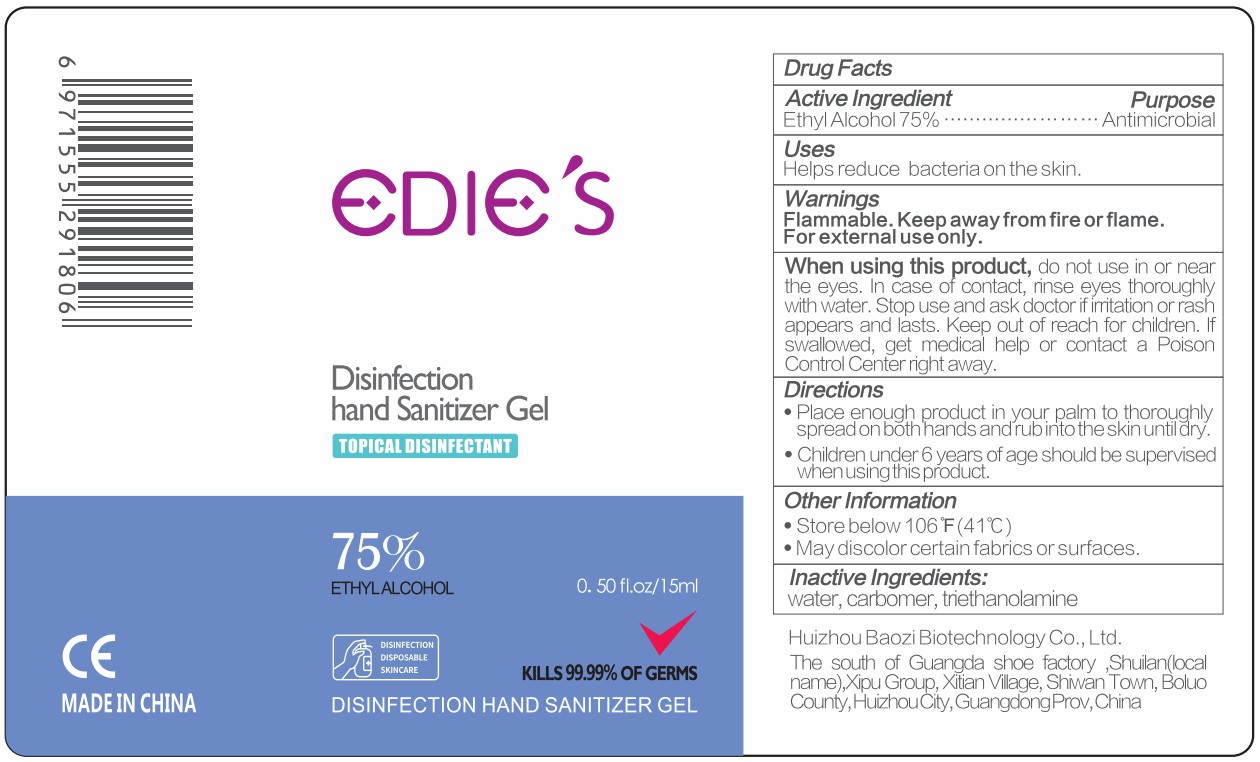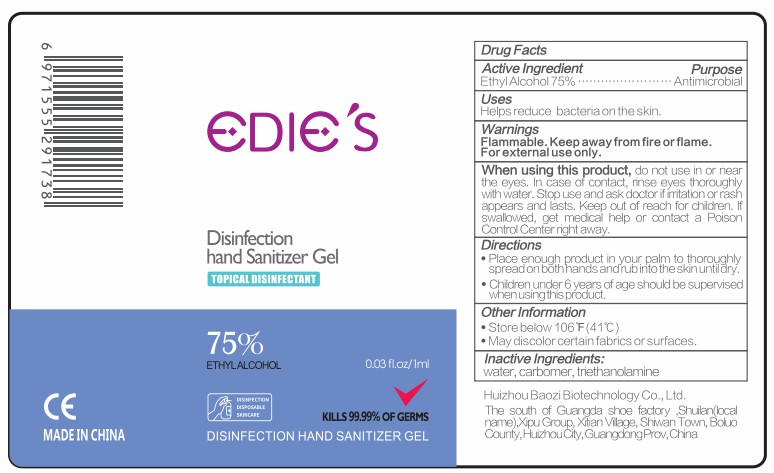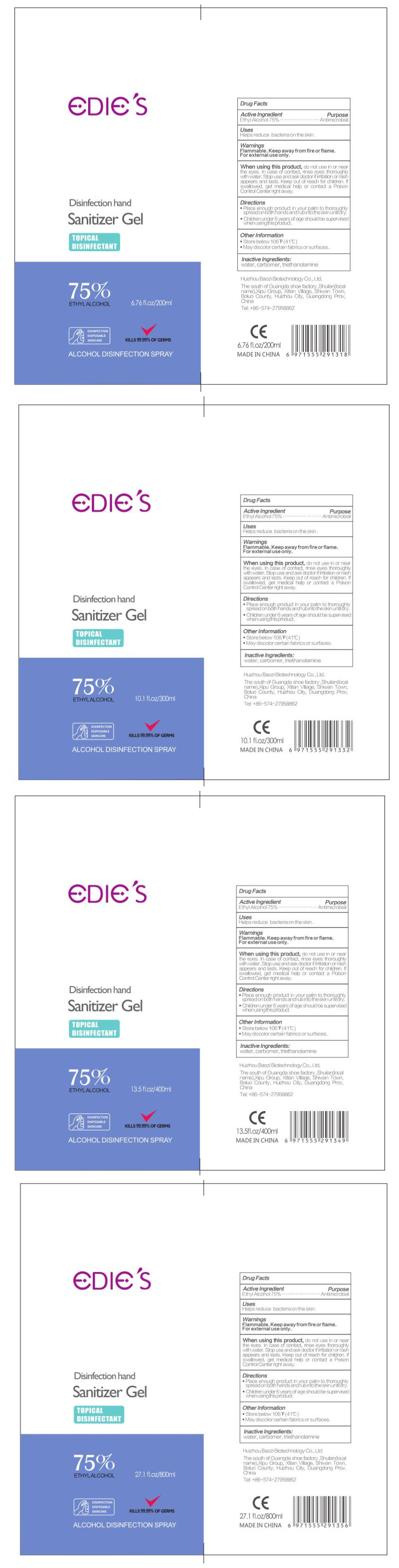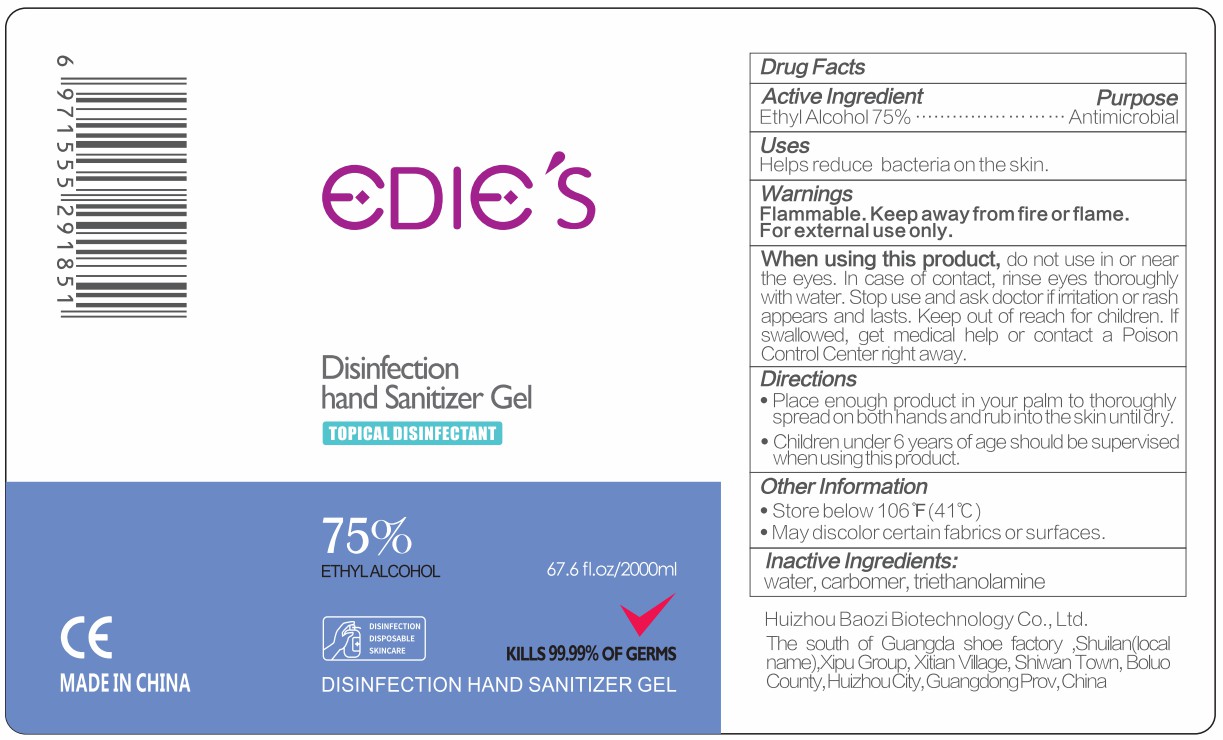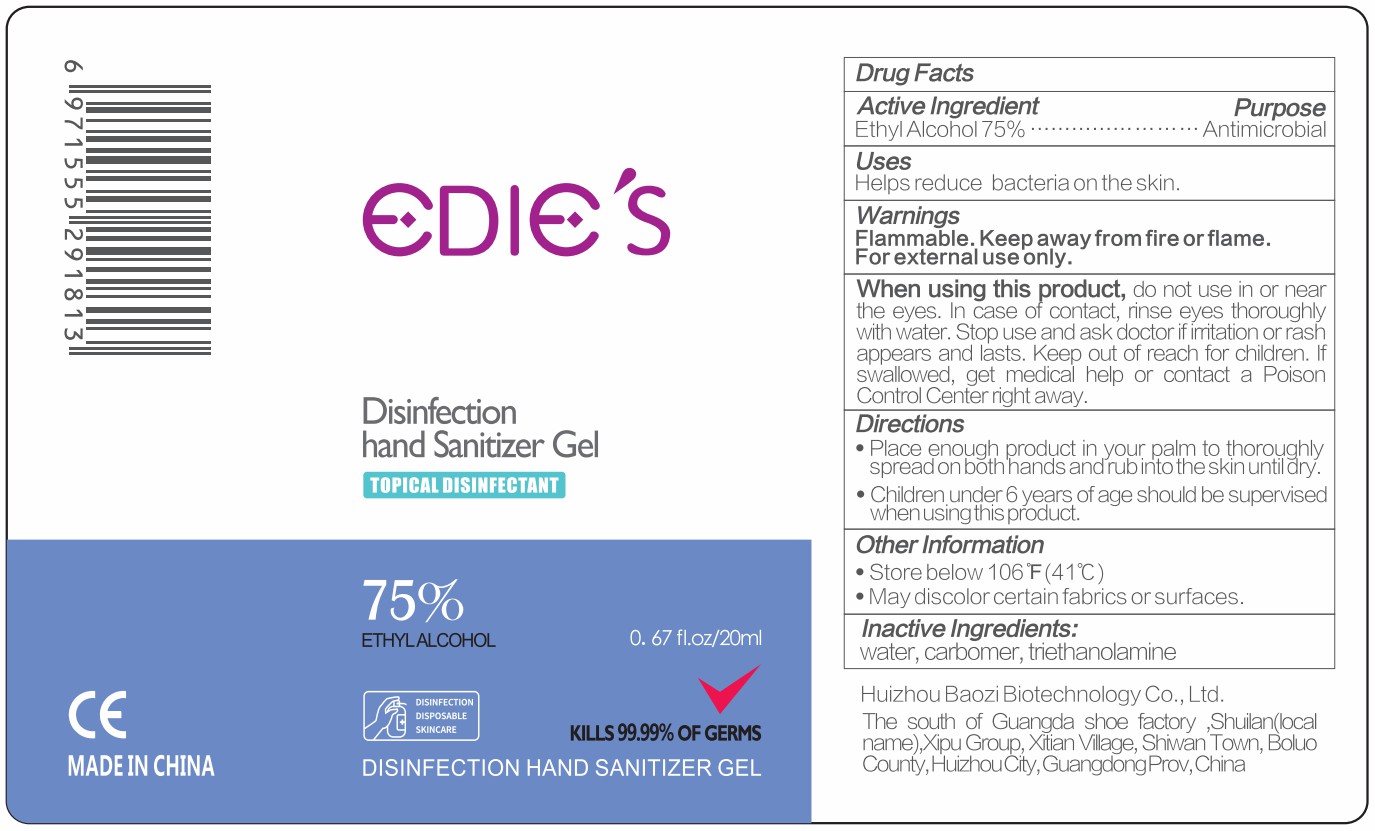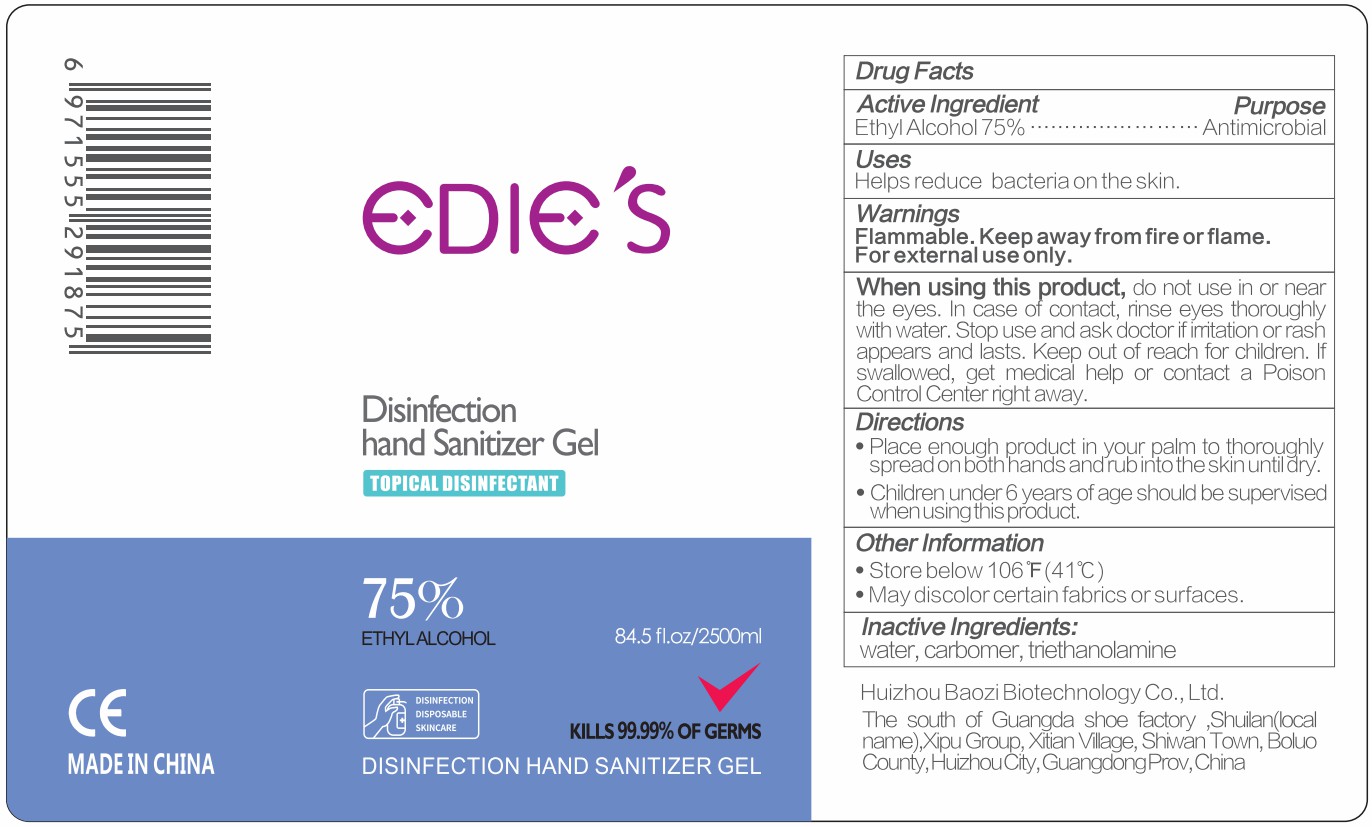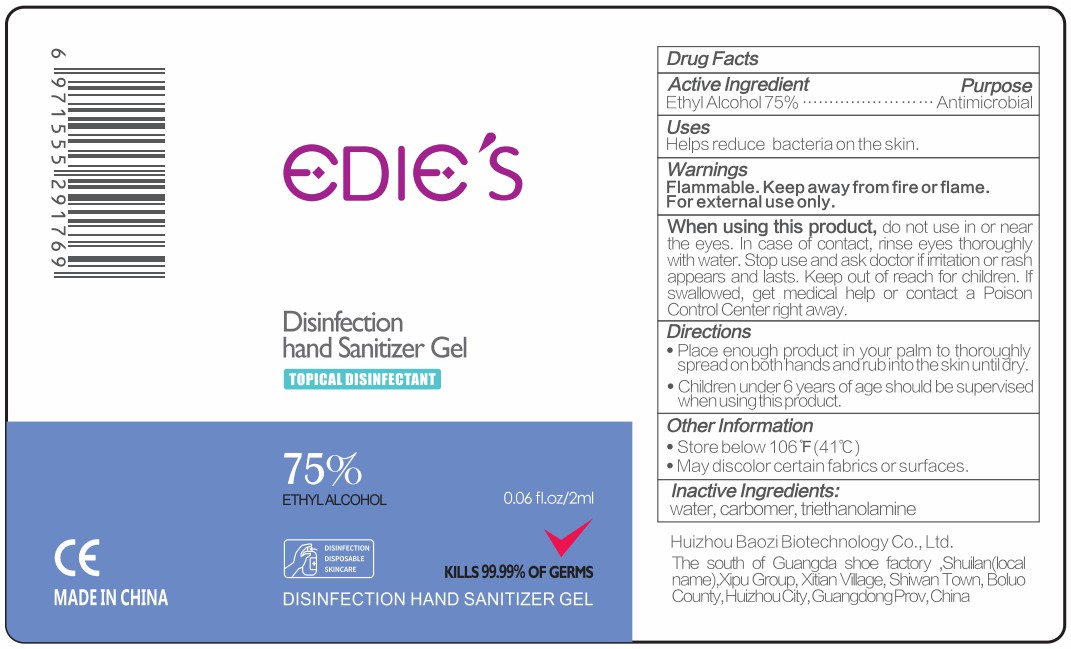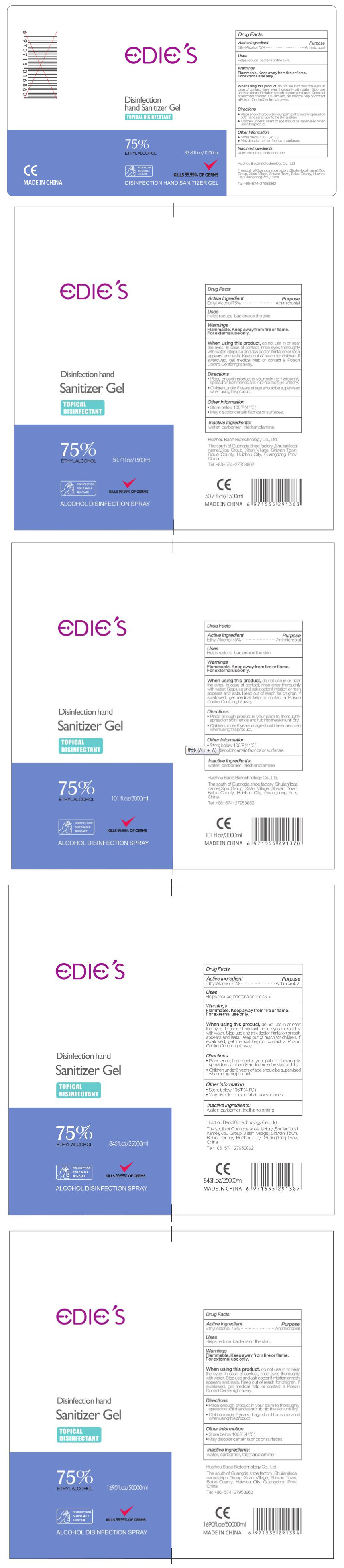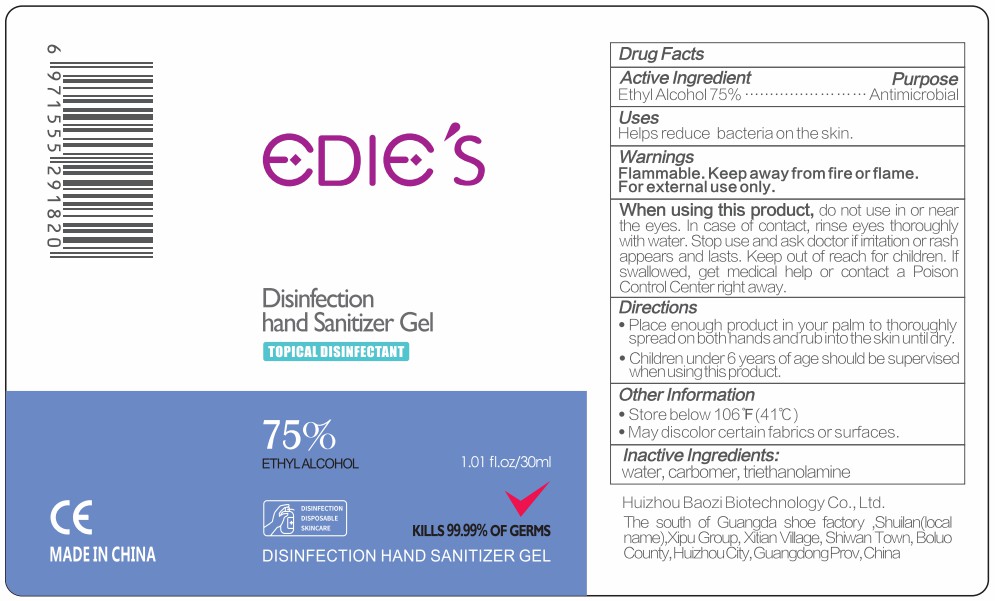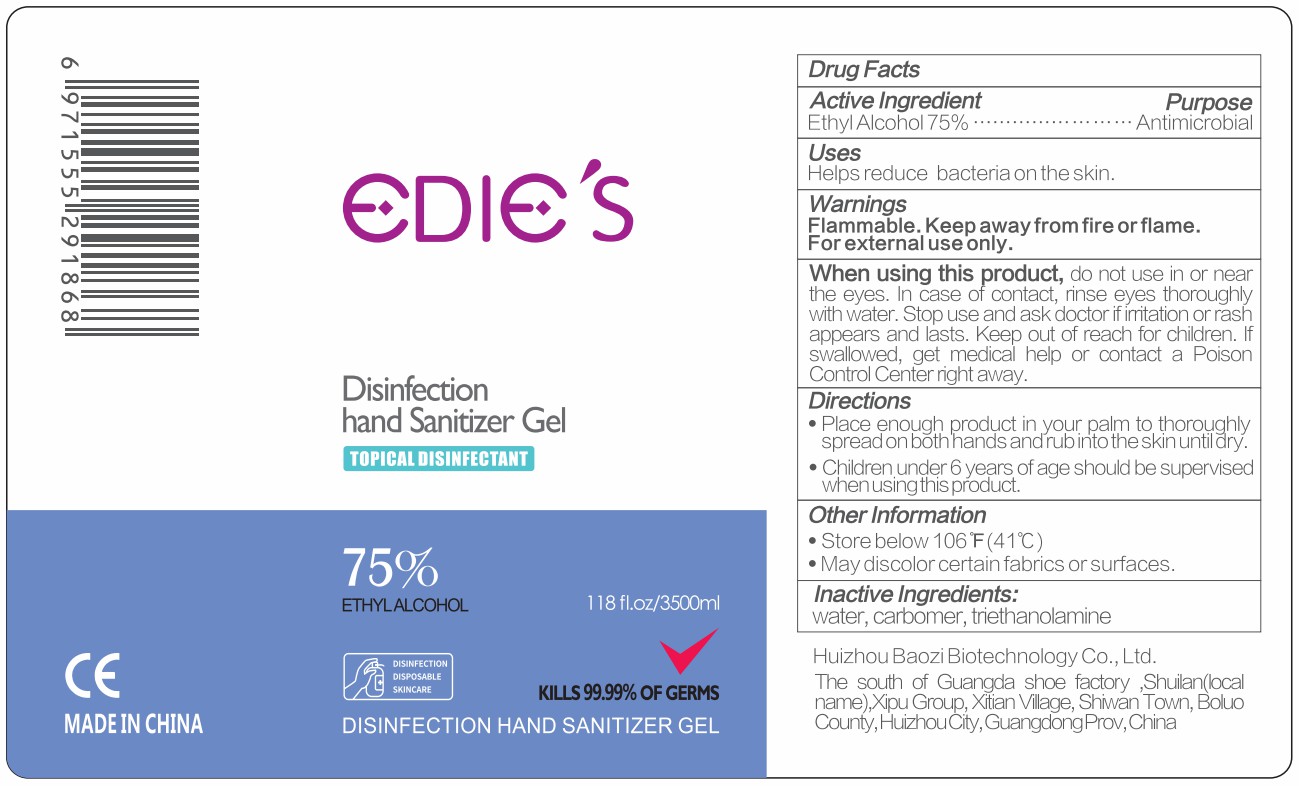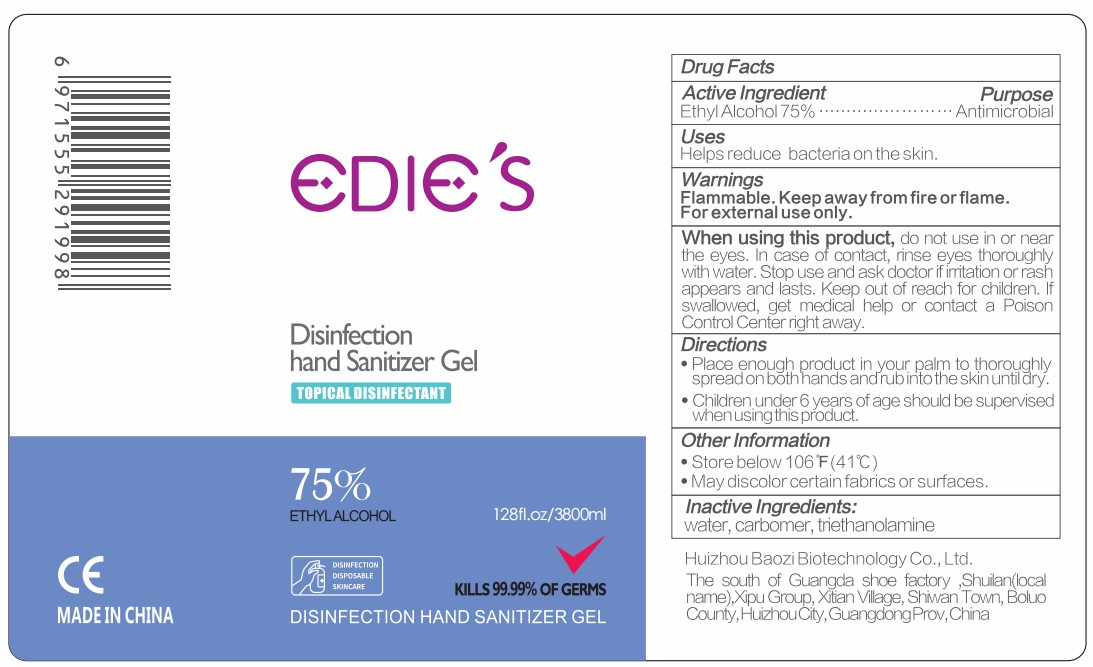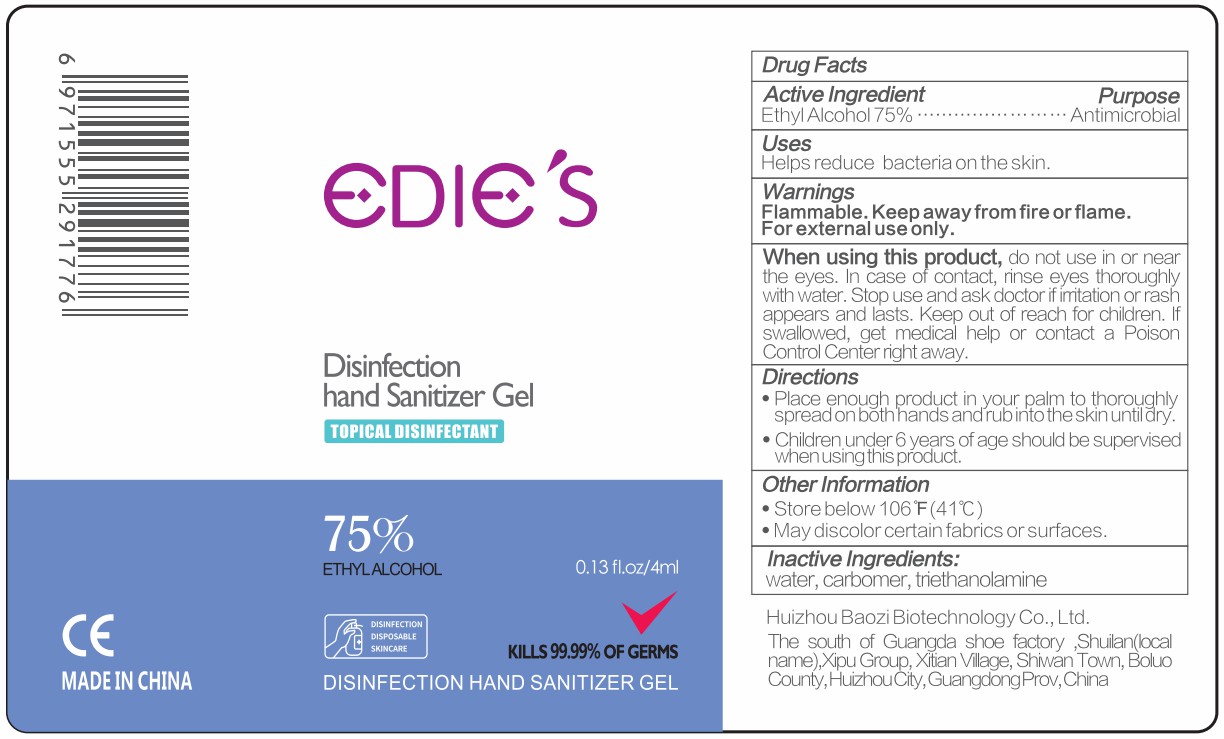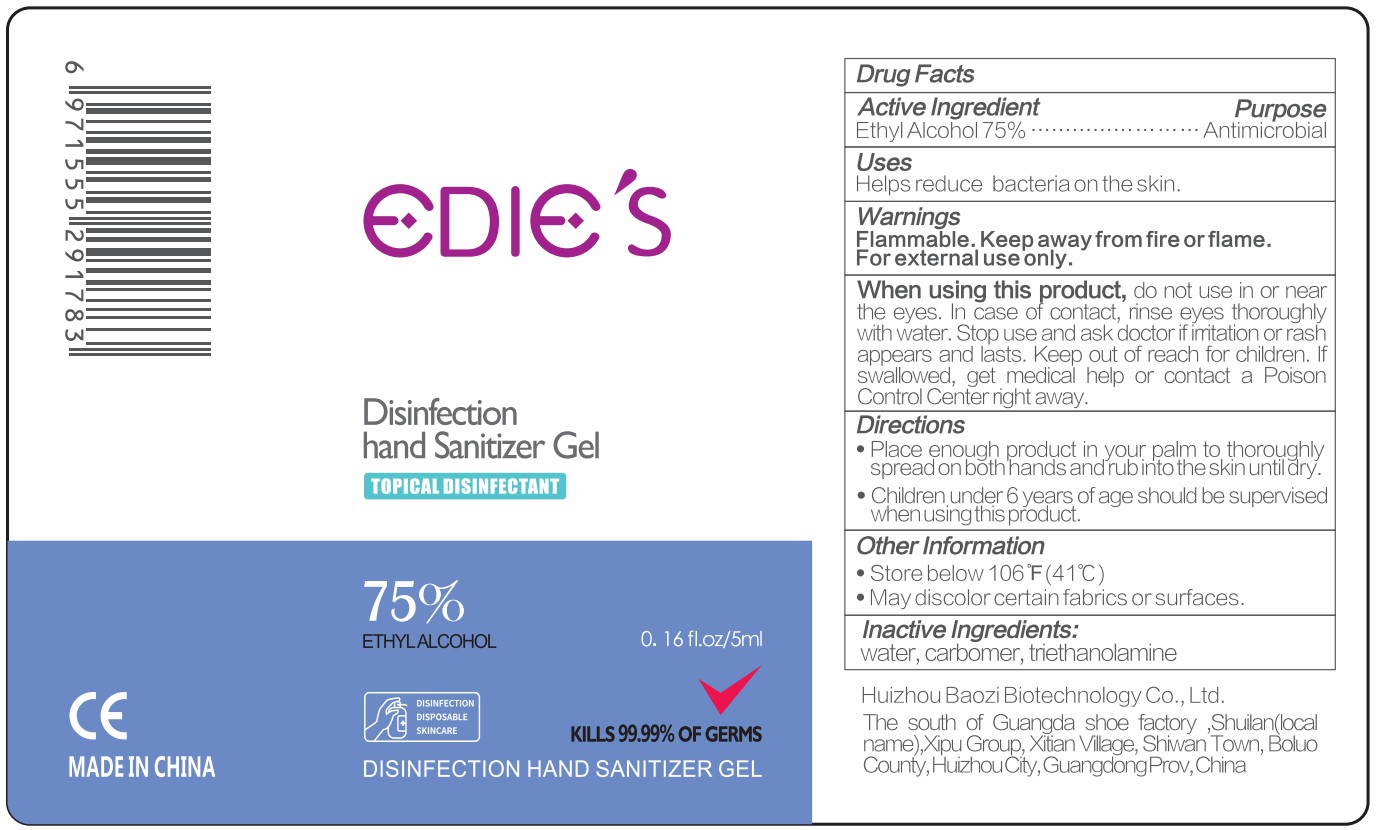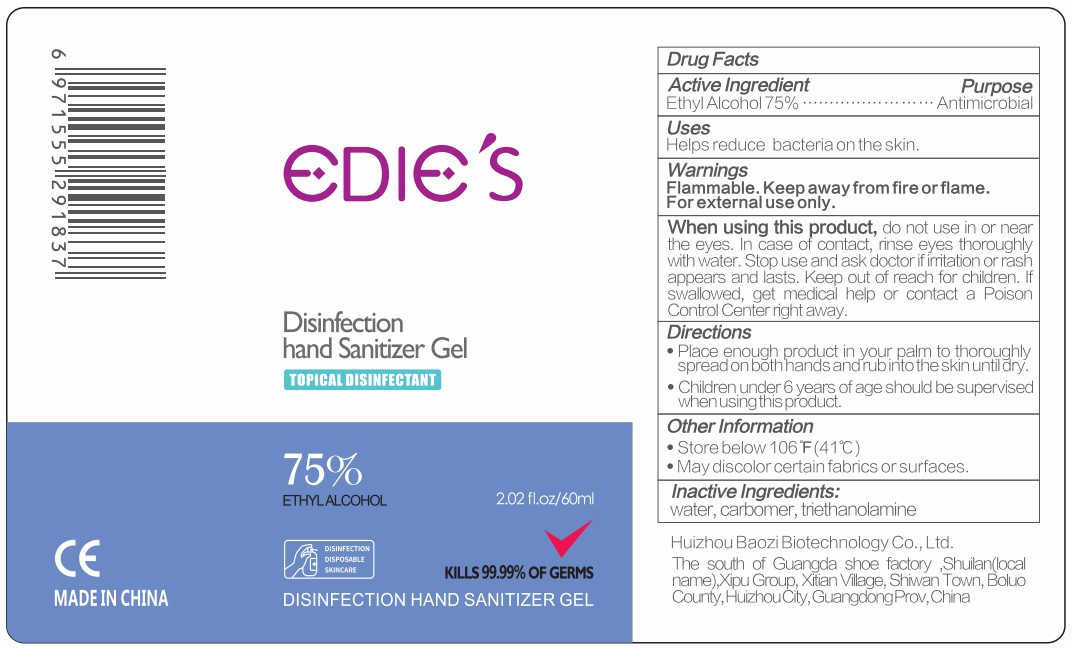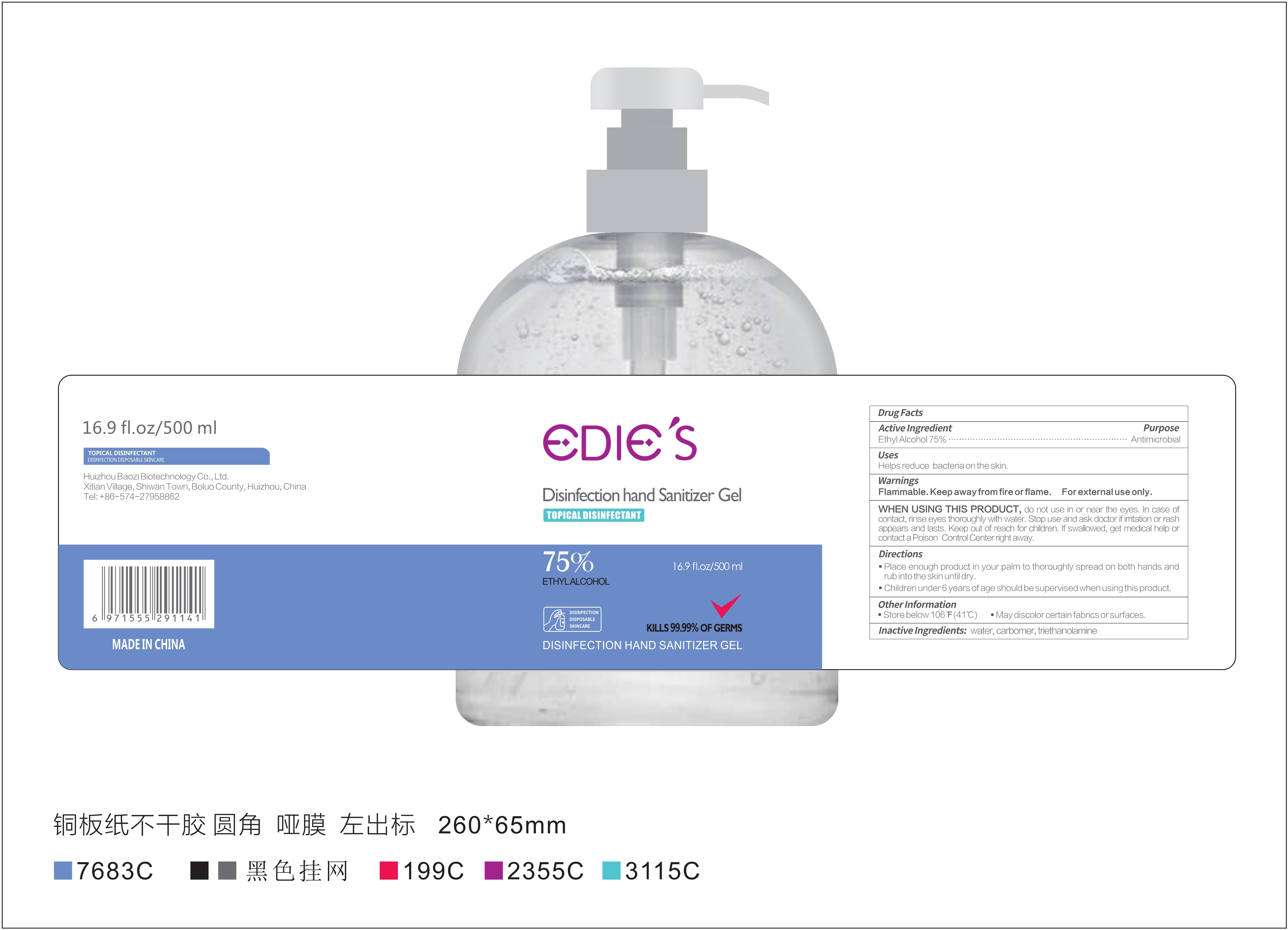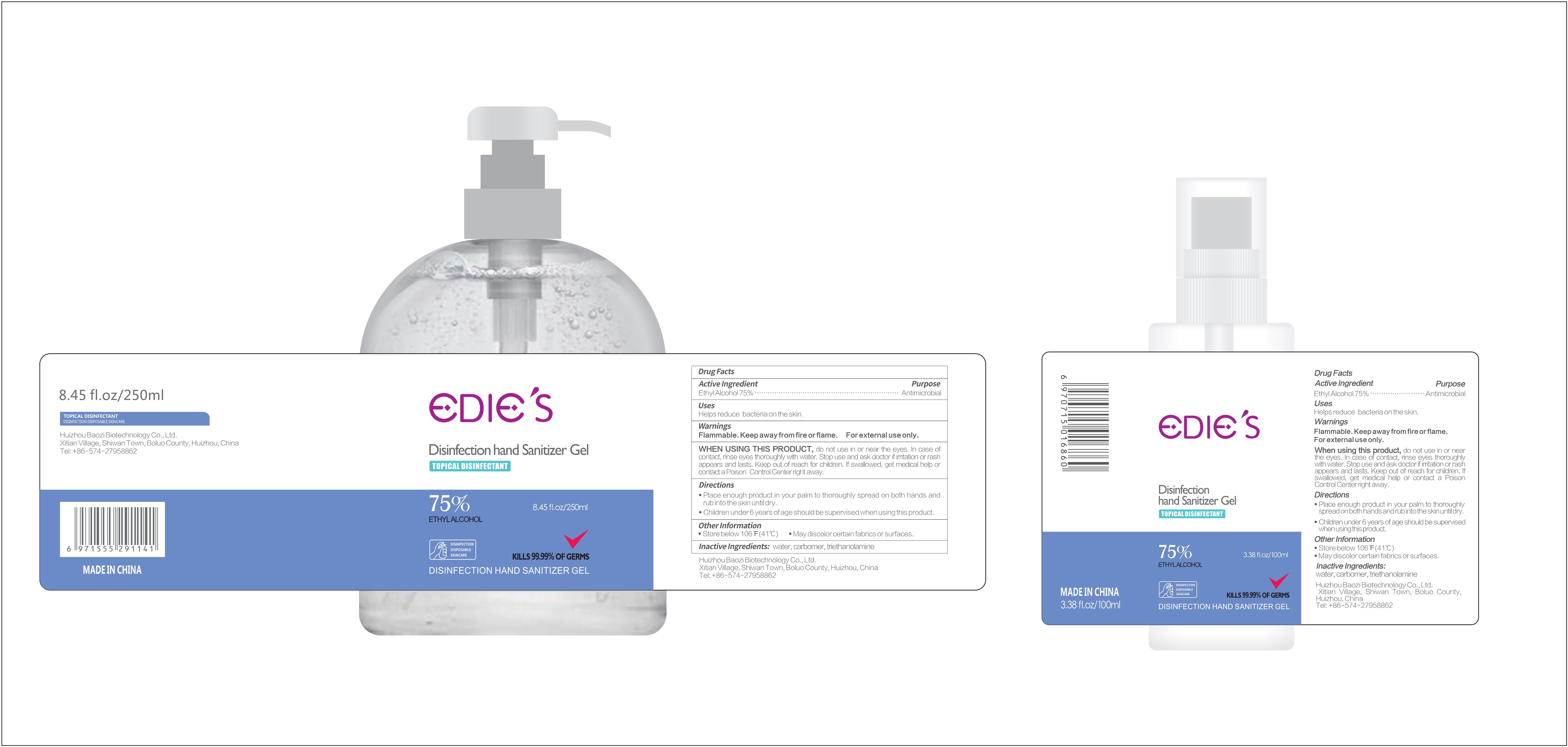 DRUG LABEL: DISINFECTION HAND SANITIZER GEl
NDC: 74881-001 | Form: GEL
Manufacturer: Huizhou Baozi Biotechnology Co., Ltd.
Category: otc | Type: HUMAN OTC DRUG LABEL
Date: 20200804

ACTIVE INGREDIENTS: ALCOHOL 75 mL/100 mL
INACTIVE INGREDIENTS: CARBOMER HOMOPOLYMER, UNSPECIFIED TYPE; WATER; TROLAMINE

74881-001 DISINFECTION HAND SANITIZER GEl

Active Ingredient

Ethyl Alcohol 75%

Purpose

Antimicrobial

Uses

Hand reduce bacteria on skin.

Warnings

Flammable. Keep away from fire or flame.For external use only.

WHEN USING THIS PRODUCT

do not use in or near the eyes.In case of contact,rinse eyes thoroughly with water.Stop use and ask doctor if irritation or rash appears and lasts.Keep out of reach for children. if swallowed,get medical help or contact a With Vitamin E& Poison Control Center right away.

Directions

Place enough Product in your palm to thoroughly spread on both hands and rub into the skin until dry.

Children under 6 years of age should be supervised when using this product.

Other information

Store below 106°F(41°C)

May discolor certain fabrics or surfaces

Inactive ingredients

Water,carbomer,triethanolamine